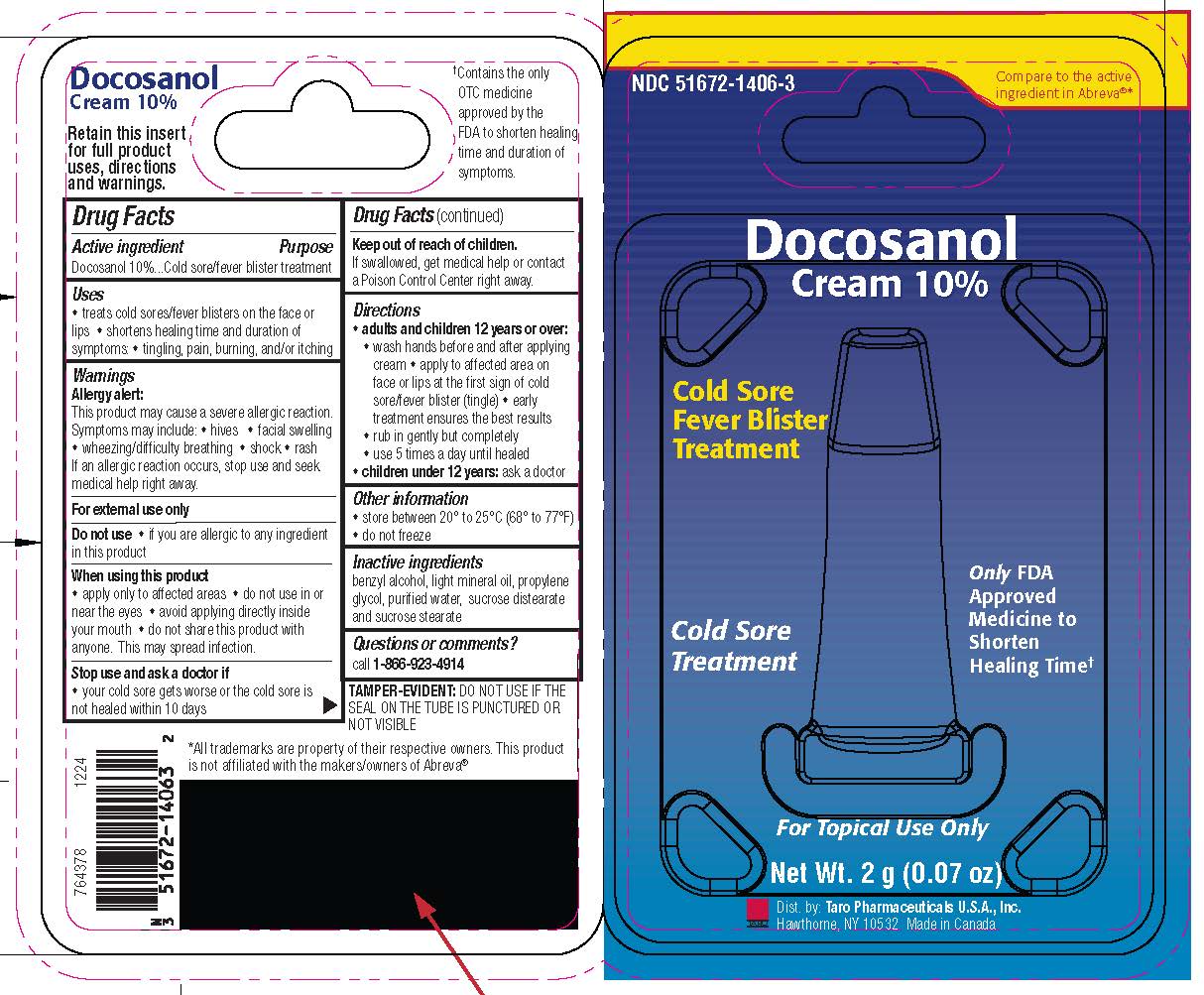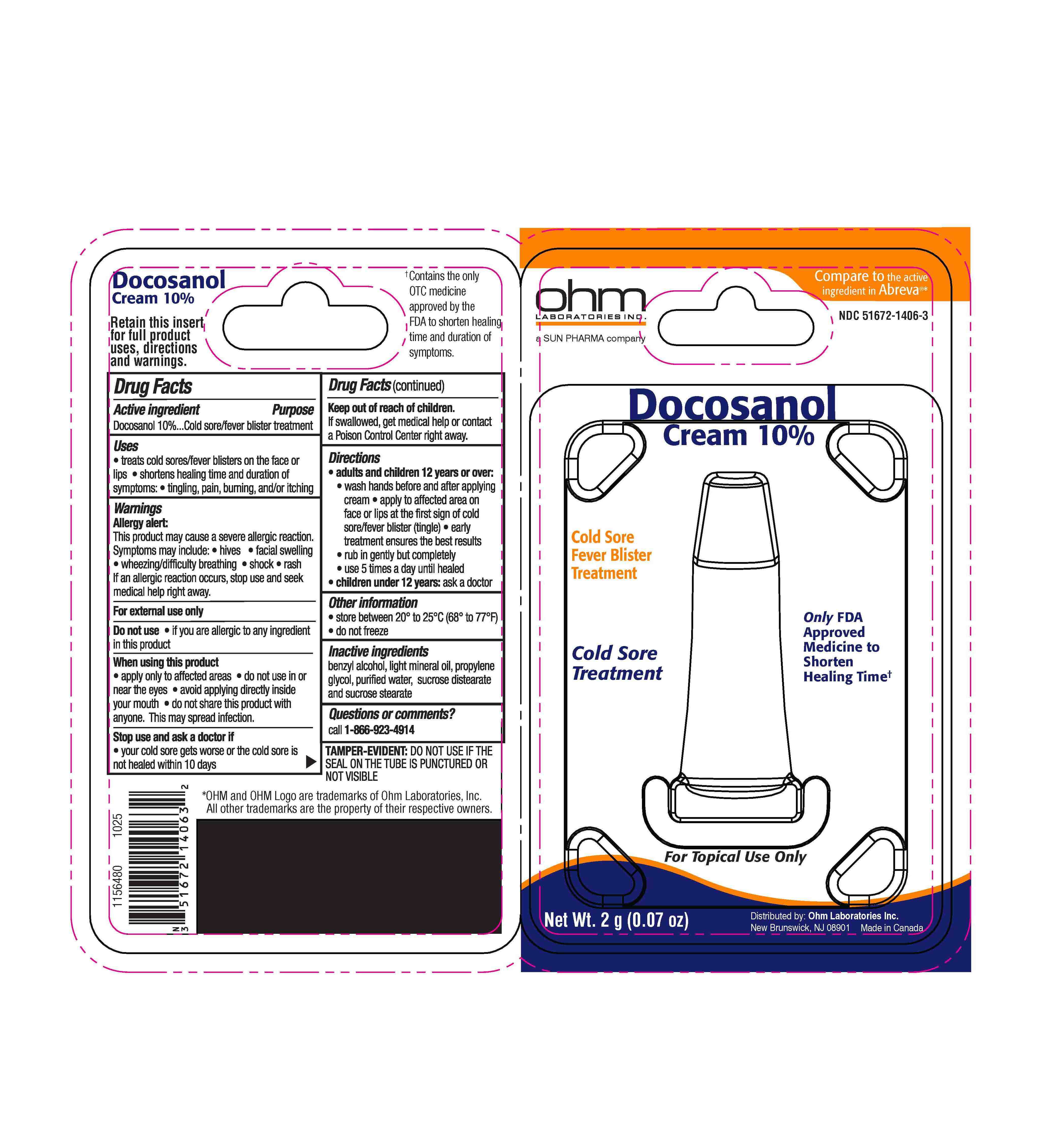 DRUG LABEL: Docosanol
NDC: 51672-1406 | Form: CREAM
Manufacturer: Sun Pharmaceutical Industries, Inc.
Category: otc | Type: HUMAN OTC DRUG LABEL
Date: 20251222

ACTIVE INGREDIENTS: DOCOSANOL 100 mg/1 g
INACTIVE INGREDIENTS: BENZYL ALCOHOL; LIGHT MINERAL OIL; PROPYLENE GLYCOL; WATER; SUCROSE STEARATE; SUCROSE DISTEARATE

Docosanol

Drug Facts

Active ingredient

Docosanol 10%

Purpose

Cold sore/fever blister treatment

Uses

- treats cold sores/fever blisters on the face or lips
- shortens healing time and duration of symptoms:
- tingling, pain, burning, and/or itching

Warnings

Allergy alert

This product may cause a severe allergic reaction. Symptoms may include:

- hives
- facial swelling
- wheezing/difficulty breathing
- shock
- rash

If an allergic reaction occurs, stop use and seek medical help right away.

For external use only

Do not use

- if you are allergic to any ingredient in this product

When using this product

- apply only to affected areas
- do not use in or near the eyes
- avoid applying directly inside your mouth
- do not share this product with anyone. This may spread infection.

Stop use and ask a doctor if

- your cold sore gets worse or the cold sore is not healed within 10 days

Keep out of reach of children.If swallowed, get medical help or contact a Poison Control Center right away.

Directions

- adults and children 12 years or over:
  - wash hands before and after applying cream
  - apply to affected area on face or lips at the first sign of cold sore/fever blister (tingle)
  - early treatment ensures the best results
  - rub in gently but completely
  - use 5 times a day until healed
- children under 12 years:ask a doctor

Other information

- store between 20° to 25°C (68° to 77°F)
- do not freeze

Inactive ingredients

benzyl alcohol, light mineral oil, propylene glycol, purified water, sucrose distearate and sucrose stearate

Questions or comments?

call 1-866-923-4914

TAMPER-EVIDENT:DO NOT USE IF THE SEAL ON THE TUBE IS PUNCTURED OR NOT VISIBLE

Dist. by: Taro Pharmaceuticals U.S.A., Inc.
Hawthorne, NY 10532

PRINCIPAL DISPLAY PANEL - 2 g Tube Package

NDC 51672-1406-3

Compare to the active
ingredient in Abreva®*

Docosanol
Cream 10%

Cold Sore
Fever Blister
Treatment

Cold Sore
Treatment

Only FDA
Approved
Medicine to
Shorten
Healing Time✝

For Topical Use Only

Net Wt. 2 g (0.07 oz)

Dist. by: Taro Pharmaceuticals U.S.A., Inc.
Hawthorne, NY 10532 Made in Canada